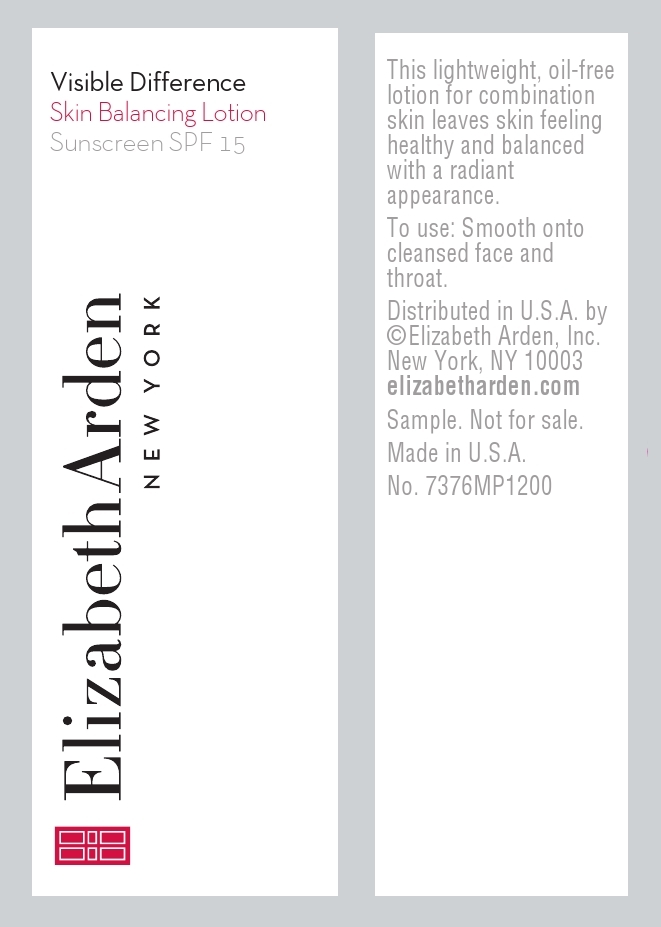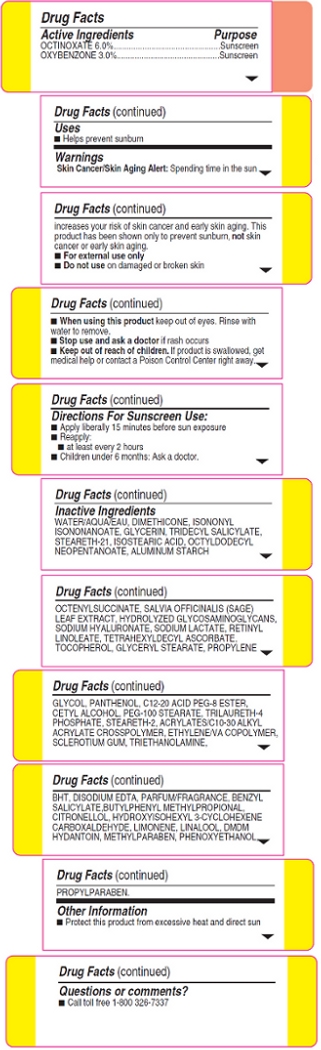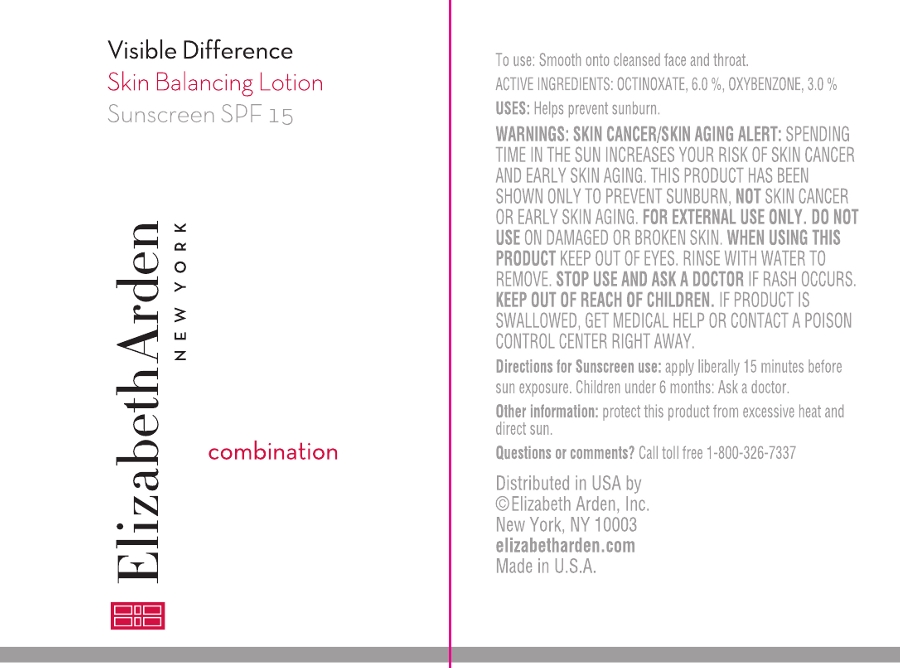 DRUG LABEL: VISIBLE DIFFERENCE SKIN BALANCING SUNSCREEN SPF 15
NDC: 67938-1000 | Form: LOTION
Manufacturer: Elizabeth Arden, Inc
Category: otc | Type: HUMAN OTC DRUG LABEL
Date: 20130501

ACTIVE INGREDIENTS: OCTINOXATE 60 mg/50 mL; OXYBENZONE 30 mg/50 mL
INACTIVE INGREDIENTS: WATER; DIMETHICONE; ISONONYL ISONONANOATE; GLYCERIN; TRIDECYL SALICYLATE; STEARETH-21; ISOSTEARIC ACID; OCTYLDODECYL NEOPENTANOATE; ALUMINUM STARCH OCTENYLSUCCINATE; SAGE; HYDROLYZED GLYCOSAMINOGLYCANS (BOVINE; 50000 MW); HYALURONATE SODIUM; SODIUM LACTATE; RETINYL LINOLEATE; TETRAHEXYLDECYL ASCORBATE; TOCOPHEROL; GLYCERYL STEARATE SE; PROPYLENE GLYCOL; PANTHENOL; PEG-100 STEARATE; TRILAURETH-4 PHOSPHATE; STEARETH-2; EDETATE DISODIUM; BENZYL SALICYLATE; BUTYLPHENYL METHYLPROPIONAL; .BETA.-CITRONELLOL, (R)-; HYDROXYISOHEXYL 3-CYCLOHEXENE CARBOXALDEHYDE; DMDM HYDANTOIN; METHYLPARABEN; PHENOXYETHANOL; PROPYLPARABEN

BB1000

DESCRIPTION

This lightweight, oil-free lotion for combination skin leaves skin feeling healthy and balanced with a radiant appearance.

INDICATIONS AND USAGE

To use: Smooth onto cleansed face and throat.

Directions For Sunscreen Use: Apply liberally 15 minutes before sun exposure. Reapply at least every 2 hours. Children under 6 months: Ask a doctor.

WARNINGS

Skin Cancer/Skin Aging Alert: Spending time in the sun increases your risk of skin cancer and early skin aging. This product has been shown only to prevent sunburn, not skin cancer or early skin aging.

For external use only

Do not use on damaged or broken skin

When using this product keep out of eyes. Rinse with water to remove.

Stop use and ask a doctor if rash occurs

OTC - ACTIVE INGREDIENT

Active Ingredients: Octinoxate 6.0 %, Oxybenzone 3.0 %

INACTIVE INGREDIENT

Inactive Ingredients: Water/Aqua/Eau, Dimethicone, Isononyl Isononanoate, Glycerin, Tridecyl Salicylate, Steareth-21, Isostearic Acid, Octyldodecyl Neopentanoate, Aluminum Starch Octenylsuccinate, Salvia Officinalis (Sage) Leaf Extract, Hydrolyzed Glycosaminoglycans, Sodium Hyaluronate, Sodium Lactate, Retinyl Linoleate, Tetrahexyldecyl Ascorbate, Tocopherol, Glyceryl Stearate, Propylene Glycol, Panthenol, C12-20 Acid PEG-8 Ester, Cetyl Alcohol, PEG-100 Stearate, Trilaureth-4 Phosphate, Steareth-2 Acrylates/C10-30 Alkyl Acrylate Crosspolymer, Ethylene/VA Copolymer, Sclerotium Gum, Triethanolamine, BHT, Disodium EDTA, Parfum/Fragrance, Benxyl Salicylate, Butylphenyl Methylpropional, Citronellol, Hydroxyisohexyl 3-Cyclohexene Carboxaldehyde, Limonene, Linalool, DMDM Hydantoin, Methylparaben, Phenoxyethanol, Propylparaben.

DOSAGE & ADMINISTRATION

Smooth on to face.

OTC - KEEP OUT OF REACH OF CHILDREN

Keep out of reach of children. If product is swallowed, get medical help or contact a Poison Control Center right away.

OTC - PURPOSE

Provides SPF 15 Sun Protection.

OTC - WHEN USING

Keep out of eyes.